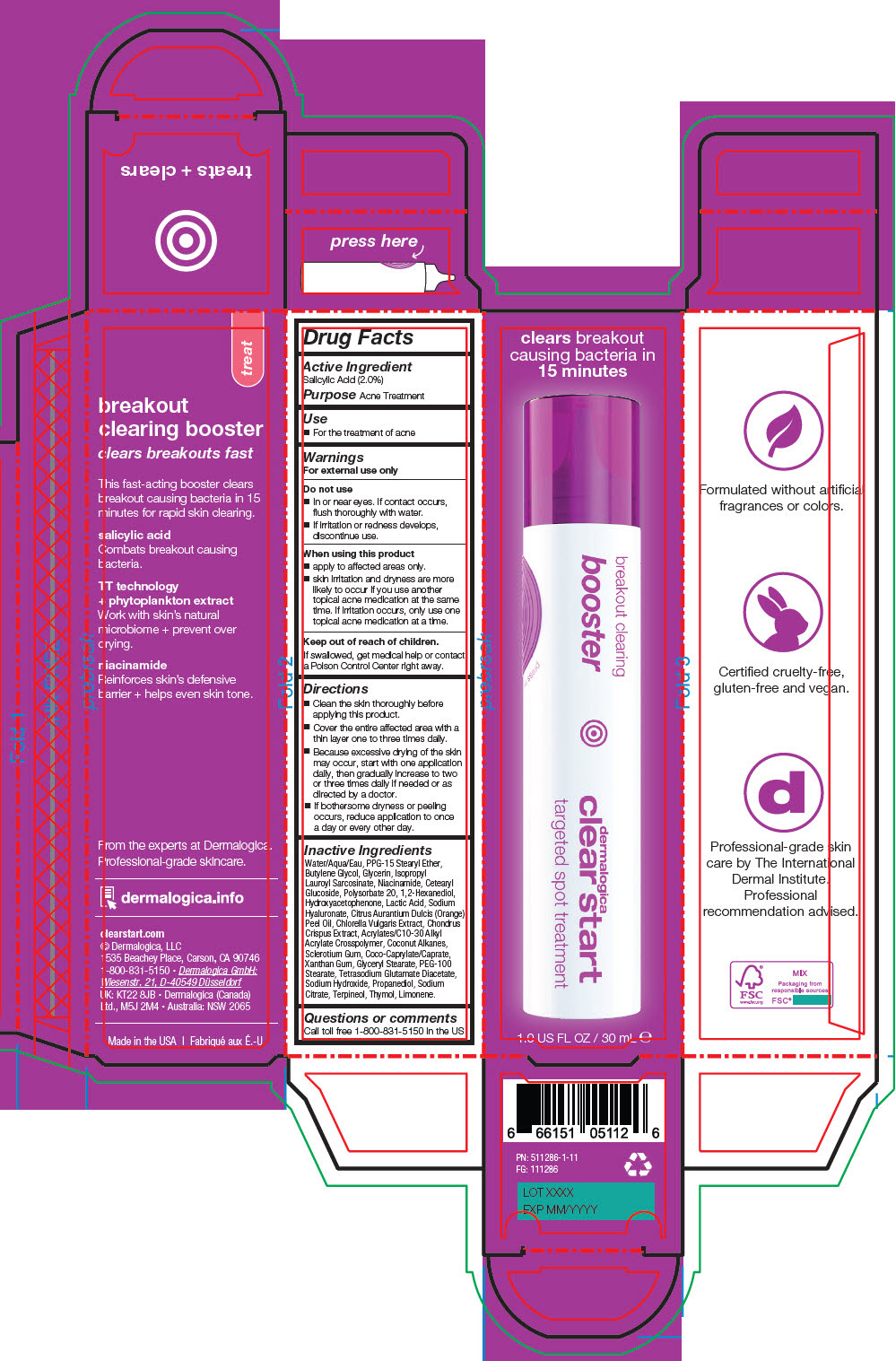 DRUG LABEL: Breakout Clearing Booster
NDC: 68479-773 | Form: LIQUID
Manufacturer: Dermalogica, LLC.
Category: otc | Type: HUMAN OTC DRUG LABEL
Date: 20251218

ACTIVE INGREDIENTS: Salicylic Acid 2 g/100 mL
INACTIVE INGREDIENTS: Water; Polypropylene Glycol 15 Stearyl Ether; Butylene Glycol; Glycerin; Isopropyl Lauroyl Sarcosinate; Niacinamide; Cetearyl Glucoside; Polysorbate 20; 1,2-Hexanediol; Hydroxyacetophenone; Coconut Alkanes; Betasizofiran; Glyceryl Monostearate; PEG-100 MONOSTEARATE; Xanthan Gum; ACRYLATES/C10-30 ALKYL ACRYLATE CROSSPOLYMER (60000 MPA.S); Propanediol; Sodium Citrate, Unspecified Form; CHONDRUS CRISPUS; Orange Oil, Cold Pressed; Terpineol; Thymol; Tetrasodium Glutamate Diacetate; Cocoyl Caprylocaprate; Chlorella Vulgaris; LACTIC ACID, DL-; Hyaluronate Sodium; Sodium Hydroxide; Limonene, (+)-

Breakout Clearing Booster

Drug Facts

Active Ingredient

Salicylic Acid (2.0%)

Purpose

Acne Treatment

Use

- For the treatment of acne

Warnings

For external use only

Do not use

- In or near eyes. If contact occurs, flush thoroughly with water.
- If irritation or redness develops, discontinue use.

When using this product

- apply to affected areas only.
- skin irritation and dryness are more likely to occur if you use another topical acne medication at the same time. If irritation occurs, only use one topical acne medication at a time.

Keep out of reach of children.

If swallowed, get medical help or contact a Poison Control Center right away.

Directions

- Clean the skin thoroughly before applying this product.
- Cover the entire affected area with a thin layer one to three times daily.
- Because excessive drying of the skin may occur, start with one application daily, then gradually increase to two or three times daily if needed or as directed by a doctor.
- If bothersome dryness or peeling occurs, reduce application to once a day or every other day.

Inactive Ingredients

Water/Aqua/Eau, PPG-15 Stearyl Ether, Butylene Glycol, Glycerin, Isopropyl Lauroyl Sarcosinate, Niacinamide, Cetearyl Glucoside, Polysorbate 20, 1,2-Hexanediol, Hydroxyacetophenone, Lactic Acid, Sodium Hyaluronate, Citrus Aurantium Dulcis (Orange) Peel Oil, Chlorella Vulgaris Extract, Chondrus Crispus Extract, Acrylates/C10-30 Alkyl Acrylate Crosspolymer, Coconut Alkanes, Sclerotium Gum, Coco-Caprylate/Caprate, Xanthan Gum, Glyceryl Stearate, PEG-100 Stearate, Tetrasodium Glutamate Diacetate, Sodium Hydroxide, Propanediol, Sodium Citrate, Terpineol, Thymol, Limonene.

Questions or comments

Call toll free 1-800-831-5150 in the US

PRINCIPAL DISPLAY PANEL - 30 mL Bottle Carton

clears breakout
causing bacteria in
15 minutes

breakout clearing
booster

dermatologica
clear start

targeted spot treatment

1.0 US FL OZ / 30 mL ℮